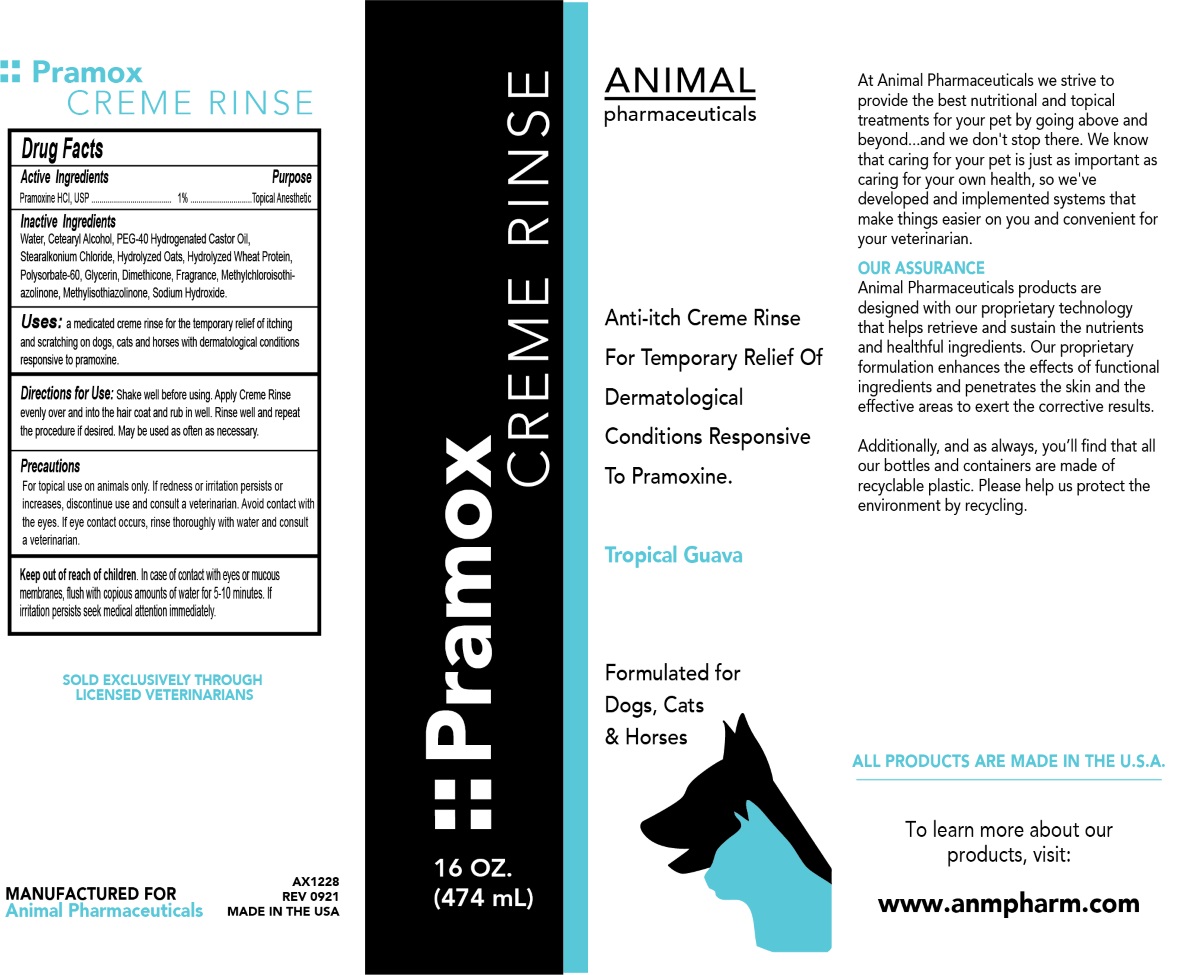 DRUG LABEL: Pramox Creme rinse
NDC: 68898-122 | Form: RINSE
Manufacturer: Animal Pharmaceuticals
Category: animal | Type: OTC ANIMAL DRUG LABEL
Date: 20211019

ACTIVE INGREDIENTS: PRAMOXINE HYDROCHLORIDE 1 g/100 mL
INACTIVE INGREDIENTS: WATER; CETOSTEARYL ALCOHOL; POLYOXYL 40 HYDROGENATED CASTOR OIL; STEARALKONIUM CHLORIDE; OAT; HYDROLYZED WHEAT PROTEIN (ENZYMATIC; 3000 MW); POLYSORBATE 60; GLYCERIN; DIMETHICONE; METHYLCHLOROISOTHIAZOLINONE; METHYLISOTHIAZOLINONE; SODIUM HYDROXIDE

Pramox CREME RINSE

Active Ingredients

Pramoxine HCl, USP 1%

Purpose

Topical Anesthetic

Inactive Ingredients

Water, Cetearyl Alcohol, PEG-40 Hydrogenated Castor Oil, Stearalkonium Chloride, Hydrolyzed Oats, Hydrolyzed Wheat Protein, Polysorbate-60, Glycerin, Dimethicone, Fragrance, Methylchloroisothiazolinone, Methylisothiazolinone, Sodium Hydroxide.

Uses:

a medicated creme rinse for the temporary relief of itching and scratching on dogs, cats and horses with dermatological conditions responsive to pramoxine.

Directions for Use:

Shake well before using. Apply Creme Rinse evenly over and into the hair coat and rub in well. Rinse well and repeat the procedure if desired. May be used as often as necessary.

Precautions

For topical use on animals only. If redness or irritation persists or increases, discontinue use and consult a veterinarian. Avoid contact with the eyes. If eye contact occurs, rinse thoroughly with water and consult a veterinarian.

Keep out of reach of children. In case of contact with eyes or mucous membranes, flush with copious amounts of water for 5-10 minutes. If irritation persists seek medical attention immediately.

Anti-itch Creme Rinse

For Temporary Relief Of Dermatological Conditions Responsive To Pramoxine.

Tropical Guava

Formulated for Dogs, Cats & Horses

At Animal Pharmaceuticals we strive to provide the best nutritional and topical treatments for your pet by going above and beyond...and we don't stop there. We know that caring for your pet is just as important as caring for your own health, so we've developed and implemented systems that make things easier on you and convenient for your veterinarian.

OUR ASSURANCE
Animal Pharmaceuticals products are designed with our proprietary technology that helps retrieve and sustain the nutrients and healthful ingredients. Our proprietary formulation enhances the effects of functional ingredients and penetrates the skin and the effective areas to exert the corrective results.

Additionally, and as always, you'll find that all our bottles and containers are made of recyclable plastic. Please help us protect the environment by recycling.

ALL PRODUCTS ARE MADE IN THE U.S.A.

To learn more about our products, visit:

www.anmpharm.com

SOLD EXCLUSIVELY THROUGH LICENSED VETERINARIANS

MANUFACTURED FOR
Animal Pharmaceuticals

MADE IN THE USA